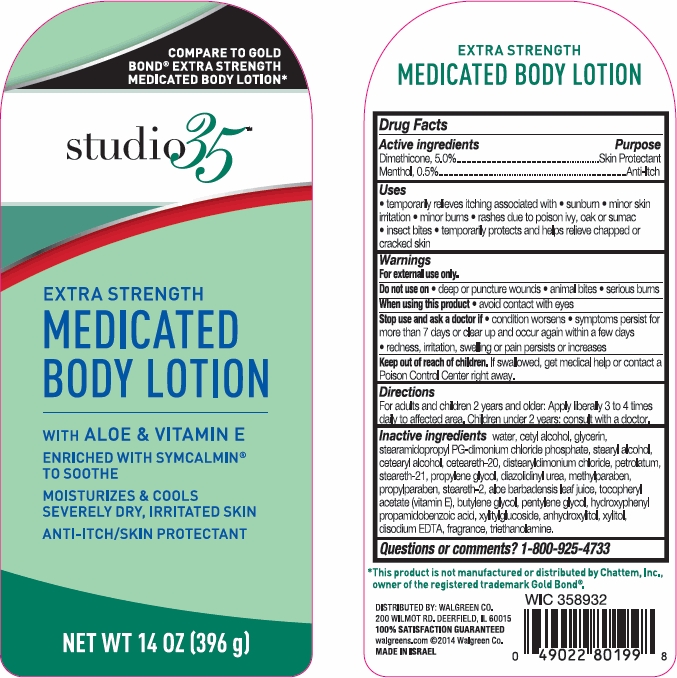 DRUG LABEL: Studio35 Extra Strength Medicated Body
NDC: 0363-8410 | Form: LOTION
Manufacturer: Walgreen Company
Category: otc | Type: HUMAN OTC DRUG LABEL
Date: 20140915

ACTIVE INGREDIENTS: DIMETHICONE 5 g/100 mL; MENTHOL 0.5 g/100 mL
INACTIVE INGREDIENTS: WATER; CETYL ALCOHOL; GLYCERIN; STEARAMIDOPROPYL PROPYLENE GLYCOL-DIMONIUM CHLORIDE PHOSPHATE; STEARYL ALCOHOL; CETOSTEARYL ALCOHOL; POLYOXYL 20 CETOSTEARYL ETHER; DISTEARYLDIMONIUM CHLORIDE; PETROLATUM; STEARETH-21; PROPYLENE GLYCOL; DIAZOLIDINYL UREA; METHYLPARABEN; PROPYLPARABEN; STEARETH-2; ALOE VERA LEAF; .ALPHA.-TOCOPHEROL ACETATE; BUTYLENE GLYCOL; PENTYLENE GLYCOL; HYDROXYPHENYL PROPAMIDOBENZOIC ACID; XYLITYLGLUCOSIDE; ANHYDROXYLITOL; XYLITOL; EDETATE DISODIUM; TROLAMINE

Walgreens Gold Max Extra Strength Medicated Body

Active ingredient

Dimethicone, 5.0%

Menthol, 0.5%

Purpose

Skin Protectant

Anti-Itch

Uses

- temporarily relieves itching associated with
  - sunburn
  - minor skin irritation
  - minor burns
  - rashes due to poison ivy, oak or sumac
  - insect bites
- temporarily protects and helps relieve chapped or cracked skin

Warnings

For external use only.

Do Not Use On

- deep or puncture wounds
- animal bites
- serious burns

When using this product

- avoid contact with eyes

Stop use and ask a doctor if

- condition worsens
- symptoms persist for more than 7 days or clear up and occur again within a few days
- redness, irritation, swelling or pain persists or increases

Keep Out of Reach of Children.

If swallowed, get medical help or contact a Poison Control Center right away.

Directions

For adults and children 2 years and older: Apply liberally 3 to 4 times daily to affected area. Children under 2 years: consult with a doctor.

Inactive ingredients

water, cetyl alcohol, glycerin, stearamidopropyl PG-dimonium chloride phosphate, stearyl alcohol, cetearyl alcohol, ceteareth-20, distearyldimonium chloride, petrolatum, steareth-21, propylene glycol, diazolidinyl urea, methylparaben, propylparaben, steareth-2, aloe barbadensis leaf juice, tocopheryl acetate (vitamin E), butylene glycol, pentylene glycol, hydroxyphenyl propamidobenzoic acid, xylitylglucoside, anhydroxylitol, xylitol, disodium EDTA, fragrance, triethanolamine.

Questions or comments?

1-800-925-4733

Package/Label Principal Display Panel

COMPARE TO GOLD
BOND® EXTRA STRENGTH
MEDICATED BODY LOTION*

studio35™

EXTRA STRENGTH
MEDICATED
BODY LOTION

WITH ALOE AND VITAMIN E

ENRICHED WITH SYMCALMIN®
TO SOOTHE

MOISTURIZES & COOLS
SEVERELY DRY, IRRITATED SKIN

ANTI-ITCH/SKIN PROTECTANT

NET WT 14 OZ (396 g)

EXTRA STRENGTH
MEDICATED BODY LOTION

*This product is not manufactured or distributed by Chattem, Inc., owner of the registered trademark Gold Bond®.

DISTRIBUTED BY: WALGREEN CO.
200 WILMOT RD. DEERFIELD, IL 60015
100% SATISFACTION GUARANTEED
walgreens.com ©2014 Walgreen Co.
MADE IN ISRAEL

Carton Label